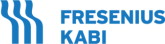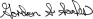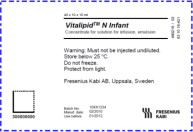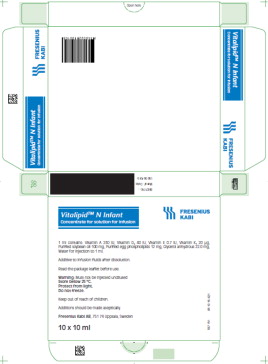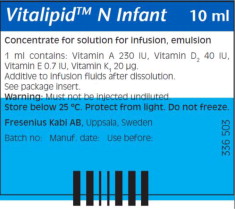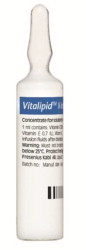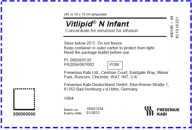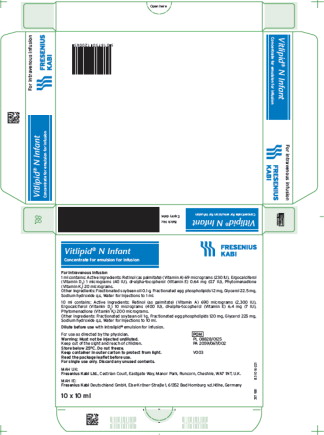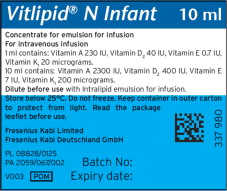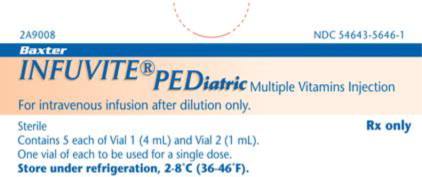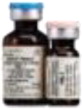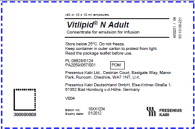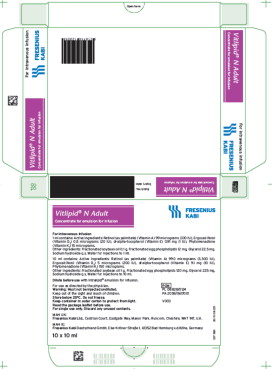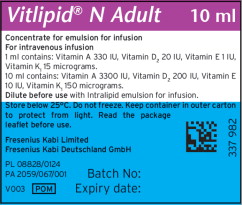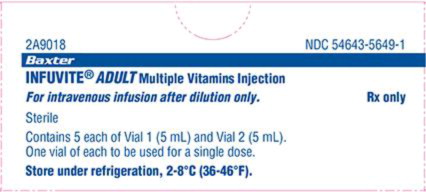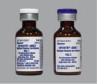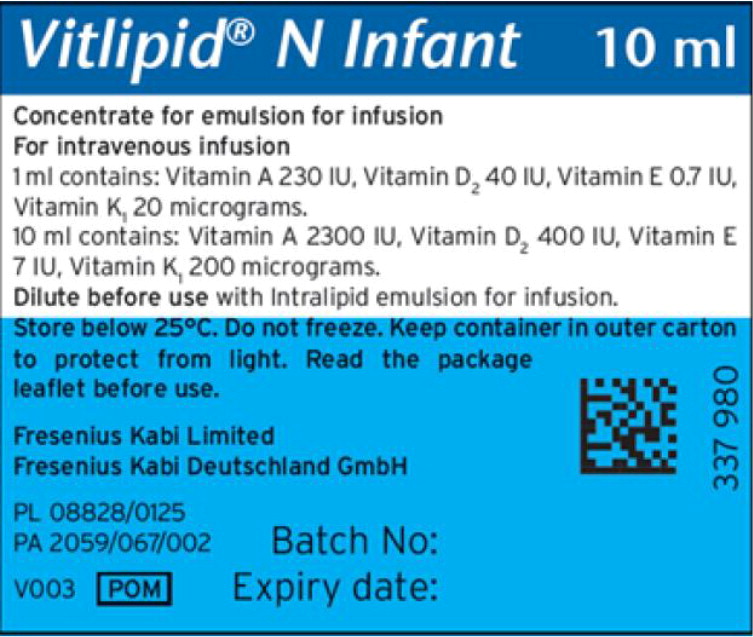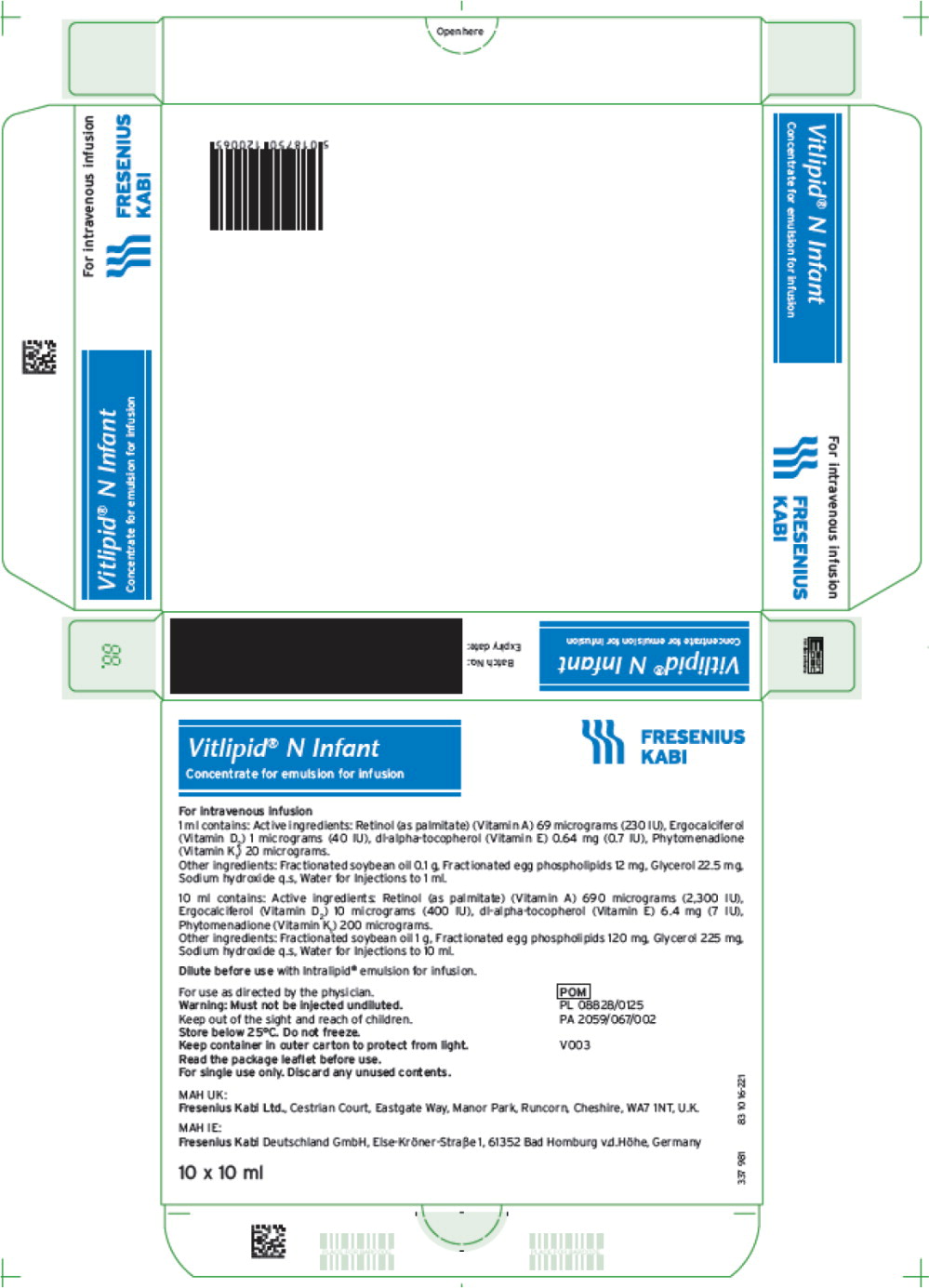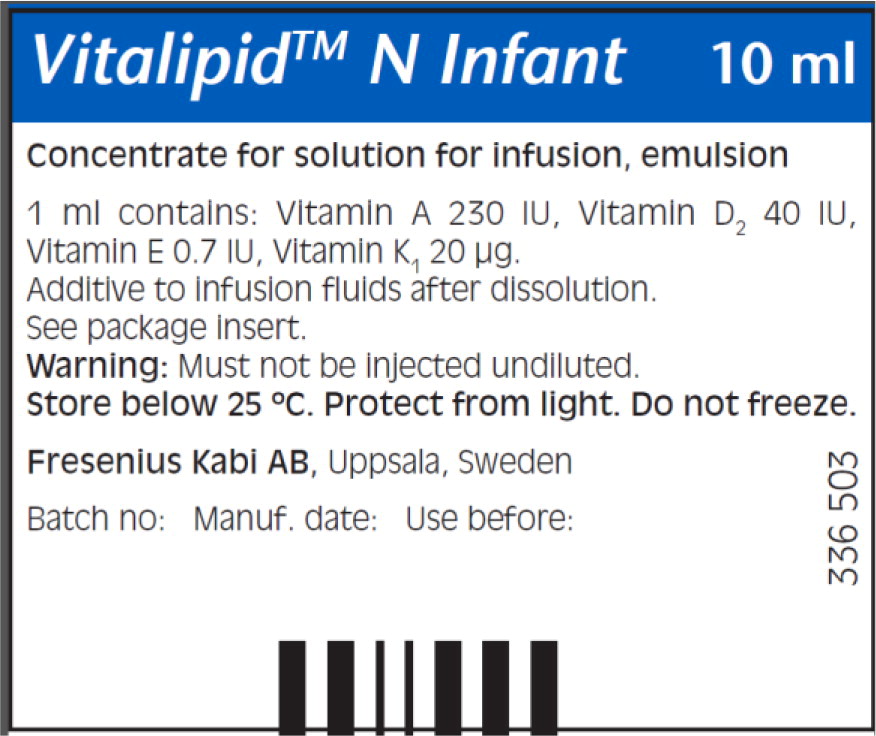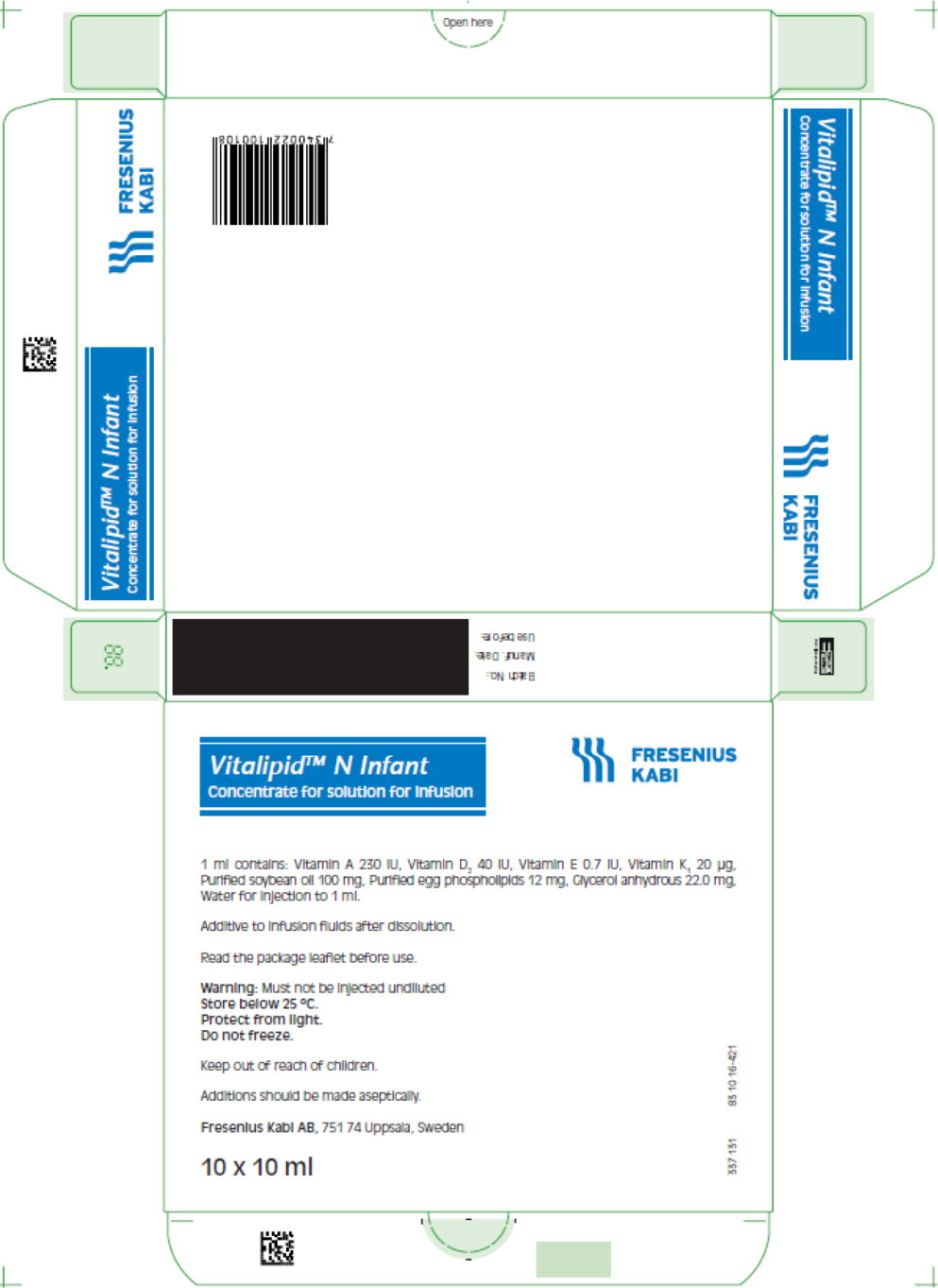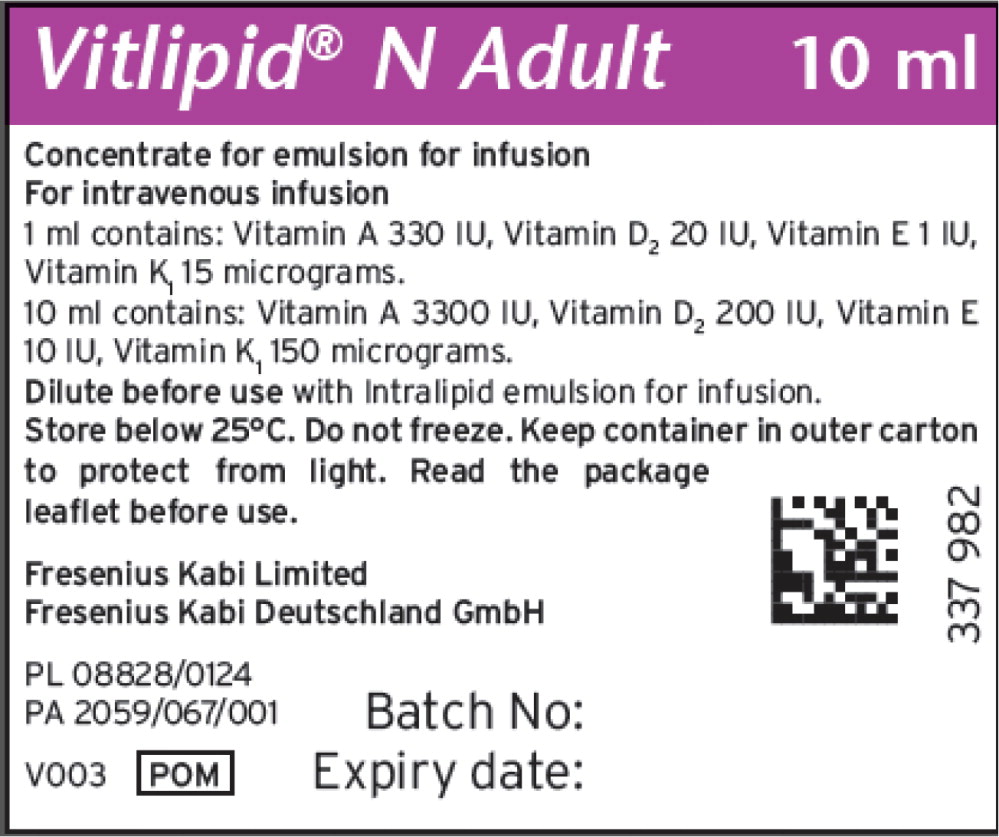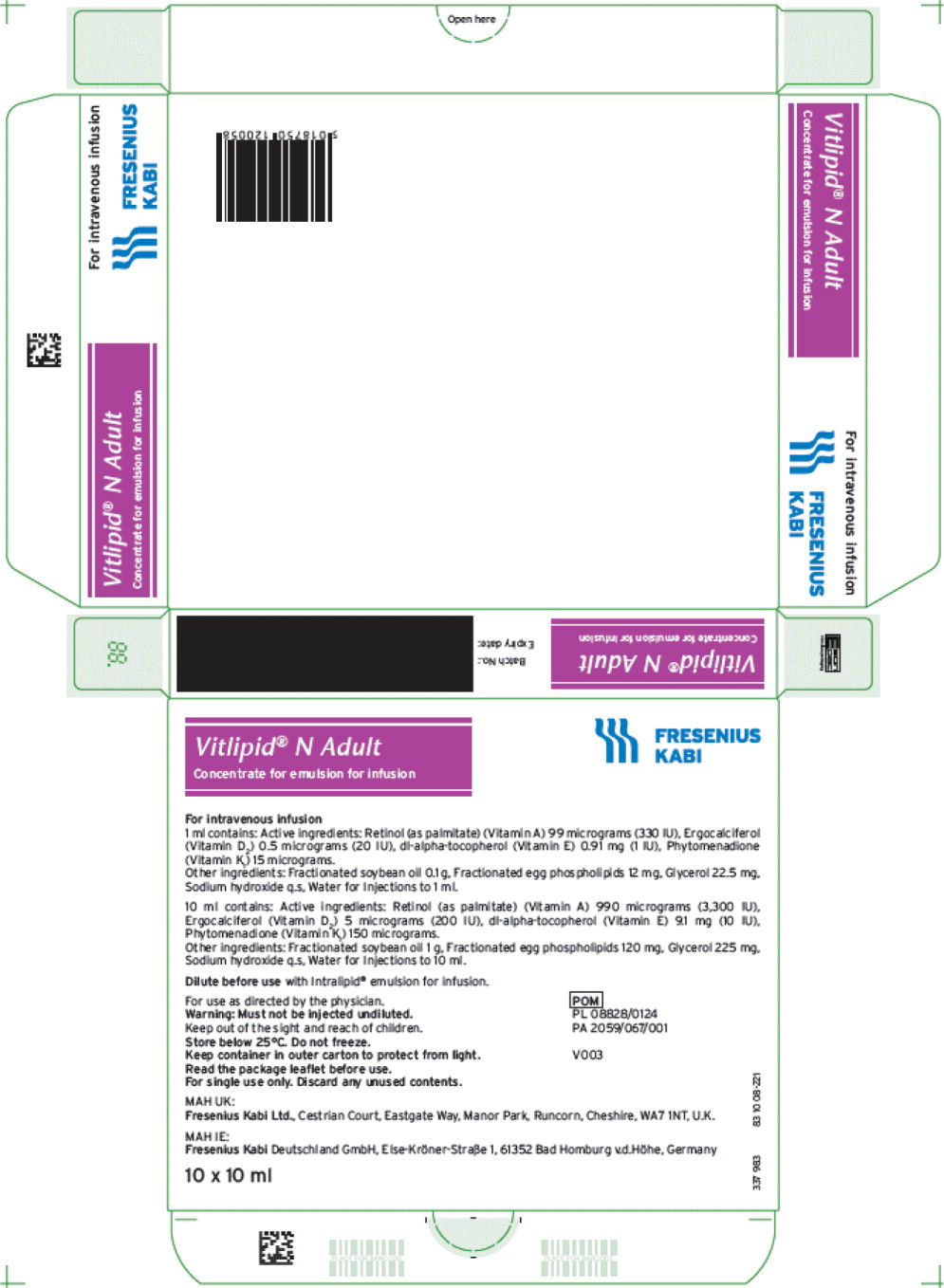 DRUG LABEL: Vitalipid N
NDC: 65219-337 | Form: EMULSION
Manufacturer: Fresenius Kabi USA, LLC
Category: prescription | Type: HUMAN PRESCRIPTION DRUG LABEL
Date: 20230907

ACTIVE INGREDIENTS: VITAMIN A PALMITATE 230 [iU]/1 mL; Ergocalciferol 40 [iU]/1 mL; .ALPHA.-TOCOPHEROL, DL- 0.7 [iU]/1 mL; PHYTONADIONE 20 ug/1 mL
INACTIVE INGREDIENTS: EGG PHOSPHOLIPIDS; GLYCERIN; SODIUM HYDROXIDE; WATER; SOYBEAN OIL

HEALTH CARE PROVIDER LETTER

Fresenius Kabi USA, LLC
Three Corporate Drive
Lake Zurich, Illinois 60047
T 847-550-2300
T 888-391-6300

September 1, 2023

www.fresenius-kabi.us

IMPORTANT PRESCRIBING INFORMATION
Subject: | Temporary importation of Vitalipid N ADULT and Vitalipid N INFANT to address drug shortage. The product is also labeled as Vitlipid N ADULT and Vitlipid N INFANT.

Dear Healthcare Professional,

Due to the critical shortage of parenteral multivitamins in the U.S. market, Fresenius Kabi USA, LLC (Fresenius Kabi USA) is coordinating with the U.S. Food and Drug Administration (FDA) to provide an alternative treatment option during this time. Fresenius Kabi USA has initiated temporary importation of Vitalipid Injection 10 mL Single Dose Glass Ampule into the U.S. market. The products imported into the U.S. may also be labeled with a slight variation of the proprietary name, Vitlipid N ADULT and Vitlipid N INFANT, depending on which country the product was originally intended. Other than the slight variation in the proprietary name, the products are identical, and the products will be referred to as Vitalipid N ADULT and Vitalipid N INFANT for the remainder of this letter. Vitalipid N ADULT and Vitalipid N INFANT are sterile oil-in-water emulsions containing fat-soluble vitamins in the oil phase. This product is marketed in Europe and is manufactured in the Fresenius Kabi Uppsala, Sweden plant.

At this time, no other entity except Fresenius Kabi USA is authorized by the FDA to import or distribute Vitalipid Injection 10 mL Single Dose Glass Ampules (One Point Cut) in the U.S. The FDA has not approved Fresenius Kabi's Vitalipid product for marketing in the United States.

This communication and product information is available on the Fresenius Kabi USA web site http://products.fresenius-kabi.us/product-323.html as well as on the FDA Drug Shortage web site. http://www.fda.gov/Drugs/DrugSafety/DrugShortages/default.htm.

IMPORTANT DRUG INFORMATION

It is important to note the following key differences between the Vitalipid and Infuvite:

Product Name | U.S. FDA-Approved Product (Infuvite Adult)^1 | Imported Product (Vitalipid N Adult)^2,3 | U.S. FDA-Approved Product (Infuvite Pediatric)^4 | Imported Product (Vitalipid N Infant)^5,6
Manufacturer | Baxter | Fresenius Kabi | Baxter | Fresenius Kabi
Indication | For prevention of vitamin deficiency in adults and children aged 11 and older receiving parenteral nutrition | Indicated in adult patients and children from 11 years of age as a supplement in intravenous nutrition to meet the daily requirements of the fat-soluble vitamins A, D2, E and K1. | For the prevention of vitamin deficiency in pediatric patients up to 11 years of age receiving parenteral nutrition | Indicated in infants and children up to 11 years of age as a supplement in intravenous nutrition to meet the daily requirements of the fat-soluble vitamins A, D2, E and K1.
Product ingredients present | 13 vitamins present (water and fat soluble) | Only 4 fat-soluble vitamins | 13 vitamins present (water and fat soluble) | Only 4 fat-soluble vitamins
Contraindications | Existing hypervitaminosis or history of hypersensitivity due to any vitamins or excipients contained in the formulation | Egg, soy, peanut allergy, hypersensitivity to ingredient/excipient | Existing hypervitaminosis or history of hypersensitivity due to any vitamins or excipients contained in the formulation | Egg, soy, peanut allergy, hypersensitivity to ingredient/excipient
Storage | Minimize exposure to light because vitamins A, D and riboflavin are light sensitive. Store under refrigeration, 2-8°C (36-46°F). | Between 2-25°C (36-77°F). Protect from light. Do not freeze | Minimize exposure to light because vitamins A, D and riboflavin are light sensitive. Store under refrigeration, 2-8°C (36-46°F). | Between 2-25°C (36-77°F). Protect from light. Do not freeze
Bar code/NDC | 54643-5649-1 | NDC (Finished Product): 6521933381; 6521933582 NDC (Unit of Use): 6521933310; 6521933510 | 54643-5646-1 | NDC (Finished Product): 6521933762; 6521933964 NDC (Unit of Use): 6521933710; 6521933910

- Vitalipid is packaged in glass ampules, so filter needles must always be used in conjunction with a regular (nonfilter) needle during compounding to reduce the risk of introducing glass particles during administration
- Vitalipid provides fat-soluble vitamins (A, D, E, K) only; Infuvite contains fat-soluble vitamins as well as 9 water-soluble vitamins (see Product Comparison Table below)
- Vitalipid N ADULT and INFANT are contraindicated in patients with known hypersensitivity to any of the components (i.e., egg, soy, peanut protein, or any active substance or excipient)
- Any barcodes on the Vitalipid N ADULT or Vitalipid N INFANT products will not be appropriately recognized by scanning systems used in the United States and should NOT be used. Institutions should manually input the product into their systems to confirm that barcode systems do not provide incorrect information when the product is scanned. Alternative procedures should be followed to assure that the correct drug product is being prepared and administered to individual patients.
- Vitalipid N ADULT and Vitalipid N INFANT are available only by prescription in the U.S. However, the imported lots do not have the statement “Rx only” on their labeling.

Effective immediately, and during this temporary period, Fresenius Kabi USA will offer the following presentation of adult and pediatric multivitamins:

Product Description

Vitalipid/Vitlipid N ADULT 10 mL^2,3
Description | Concentrated Emulsion for Injection
Dosage Form: | 10 mL Single Dose Glass Ampule
Package size | Box contains 10 units of 10 mL
Finished Product NDC | 6521933582
Unit of Use NDC | 6521933510
Lot Numbers/(Expiration Date) | 10SC1307/(2025.02.28); 10SD2190 (2025.03.31)
Vitamin | Active Ingredients (per 1 mL) | Active Ingredients (per 10 mL)
Retinol palmitate (Vitamin A) | 99 mcg (330 IU) | 990 mcg (3300 IU)
Ergocalciferol (Vitamin D 2) | 0.5 mcg (20 IU) | 5 mcg (200 IU)
All-rac-alpha-tocopherol (Vitamin E) | 0.91 mg (1IU) | 9.1 mg (10 IU)
Phytomenadione (Vitamin K 1) | 15 mcg | 150 mcg
 | Excipients (per 1 mL) | Excipients (per 10 mL)
Purified egg phospholipids | 12 mg | 120 mg
Glycerol anhydrous | 22 mg | 220 mg
Purified soybean oil | 100 mg | 1000 mg
Sodium hydroxide | N/A | To pH 8
Water for injection | N/A | To 1 mL

Vitalipid/Vitlipid N INFANT 10 mL^5,6
Description | Concentrated Emulsion for Injection
Dosage Form: | Single Dose Glass Ampule
Package Size: | Box contains 10 units of 10 mL
Finished Product NDC: | 6521933762; 6521933964
Unit of Use NDC: | 6521933710; 6521933910
Lot Numbers/(Expiration Date) | 10SB9030/(2025.01.31); 10SB9028/(2025.03.31)
Vitamin | Active Ingredients (per 1 mL) | Active Ingredients (per 10 mL)
Retinol palmitate (Vitamin A) | 69 mcg (230 IU) | 690 mcg (2300 IU)
Ergocalciferol (Vitamin D 2) | 1 mcg (40 IU) | 10 mcg (400 IU)
All-rac-alpha-tocopherol (Vitamin E) | 0.64 mg (0.7 IU) | 6.4 mg (7 IU)
Phytomenadione (Vitamin K 1) | 20 mcg | 200 mcg
 | Excipients (per 1 mL) | Excipients (per 10 mL)
Purified egg phospholipids | 12 mg | 120 mg
Glycerol anhydrous | 22 mg | 220 mg
Purified soybean oil | 100 mg | 1000 mg
Sodium hydroxide | N/A | To pH 8
Water for injection | N/A | To 1 mL

Preparation/Administration

- Vitalipid N ADULT must be diluted before use and strict aseptic technique must always be maintained during handling. Because Vitalipid N ADULT is packaged in a glass ampule, a filter needle must always be used in conjunction with a regular (nonfilter) needle during compounding to reduce the risk of introducing glass particulates during administration.
- Both Vitalipid N ADULT and Vitalipid N INFANT are packaged in One Point Cut (OPC) ampules. OPC ampules are manufactured with a colored dot on the bulbous part of the ampule indicating the position where the ampule should be broken. Please follow the recommended instructions below to open the OPC ampule easily and safely:
  - Before an ampule is opened, any solution visible in the top portion (i.e., the head) should be moved to the bottom (i.e., body) by swirling the ampule in an upright position, tapping the ampule with one's finger, or inverting the ampule and then quickly swinging it into an upright position.
  - To open an ampule properly, the head should be cleansed with an alcohol swab. The alcohol swab can be left in place or a new alcohol-soaked gauze pad can be applied to prevent accidental cuts to the fingers as well as shattering of glass particles and aerosolized drug.
  - Pick up the ampule and hold its lower part (body) between your thumb and index finger and position the ampule so that the colored dot faces you.
  - Grasp the top of the ampule with your other hand. Place your thumb over the colored dot and index finger on the opposite side (back) of the bulbous part of the ampule.
  - Hold the bottom of the ampule firmly in an upright position and push away from oneself in a quick motion to “snap” open the ampule at the neck.
  - Ampules should NOT be opened toward the HEPA filter in the compounding work area (to prevent spraying of liquid) or toward other sterile preparation within the hood.
- A regular needle should be used to withdraw 10 mL from one ampule. The regular needle should be removed from the syringe and replaced with a new filter needle to inject the 10 mL of Vitalipid into 500 mL of Intralipid (Fresenius Kabi). To ensure a homogeneous admixture, the bag should be inverted a couple of times immediately before the infusion. Vitalipid N ADULT is also used as a complement in parenteral nutrition (PN) formulations. Questions about compatibility may be directed to Fresenius Kabi USA, LLC Medical Affairs.
- Vitalipid N ADULT should be added to an infusion within one hour of administration and the infusion should be completed within 24 hours from preparation to prevent microbiological contamination. Any remaining contents of opened ampules should be discarded.
- Vitalipid N ADULT has been tested in PN formulations available outside of the U.S. containing lipid injectable emulsions under European standards and demonstrated compatibility with non-U.S. approved amino acids and other PN products. Branded U.S. PN products tested that have shown compatibility are SMOFlipid and Kabiven. Similar tests have not been conducted using U.S. amino acid products, thus caution should be taken when adding Vitalipid N ADULT to adult PN formulations. Vitalipid has also demonstrated compatibility when added to Kabiven in combination with some US amino acid branded products (e.g., Travasol 10% [Baxter Healthcare], Aminosyn II 15% [Hospira, Inc], Clinisol 15% [Baxter Healthcare], Prosol 20% [Baxter Healthcare]).
- Vitalipid N INFANT must be diluted before use in Intralipid 20% (Fresenius Kabi). The daily dose must not exceed 10 mL. Because Vitalipid N INFANT is packaged in a glass ampule, a filter needle must always be used in conjunction with a regular (nonfilter) needle during compounding to reduce the risk of introducing glass particulates during administration. A regular needle should be used to withdraw up to 10 mL from 1 ampule. The regular needle should be removed from the syringe and replaced with a new filter needle to inject up to 10 mL of Vitalipid N INFANT into Intralipid 20% (Fresenius Kabi). To ensure a homogeneous admixture, the bag should be inverted a couple of times immediately before the infusion. After mixing by gentle agitation, the emulsion is infused as described for Intralipid (Fresenius Kabi). Any remaining contents of opened ampules should be discarded.
- Vitalipid N INFANT has been tested in PN formulations available outside of the U.S. containing lipid injectable emulsions under European standards and demonstrated compatibility with non-U.S. approved pediatric amino acids and other PN products. Similar tests have not been conducted using U.S. amino acid products, thus caution should be taken when adding Vitalipid N INFANT to pediatric PN formulations. Branded U.S. PN products that have been tested and demonstrate compatibility include SMOFlipid, Intralipid (Fresenius Kabi).
- Results from stability studies show that unopened ampules of Vitalipid N ADULT and Vitalipid N INFANT can be stored both at +5±3°C and at +25°C/60 % RH for 24 months. Based on available data, the product is proposed to be stored between 2°C – 25°C with a shelf life of 24 months. Do not freeze. Protect the product from light
- Storage with dilution and admixture: The admixing of Vitalipid N ADULT and Vitalipid N INFANT in PN formulations has been investigated according to standard methods, documenting the physicochemical stability of admixtures after storage times up to 7 days. Vitalipid N ADULT and Vitalipid N INFANT have been tested with a variety of PN products marketed in the US, including Kabiven, PeriKabiven, and Intralipid 20% (Fresenius Kabi). The storage time and conditions specifically investigated compatibility of these products for 7 days, i.e., 6 days storage at 2°C -8°C followed by 24 hours at 20°C-25°C (i.e., 6+1 conditions). The methods employed are measurement of mean droplet size, droplet size distribution, pH, visual inspection and investigations aiming to determine precipitation in the aqueous phase. The latter have been carried out by comparisons with the corresponding aqueous systems without added lipid emulsion. The experimental results demonstrate that all tested compositions are stable and compatible under 6+1 conditions. It is important to note that there is variability in the U.S. use of different PN components which may not have been tested. If HCPs have specific questions based on their PN admixtures, the Fresenius Kabi Medical Information department can provide them with the information on the specific admixtures tested.
- Consult Fresenius Kabi for further information on complete and balanced intravenous nutrition regimens.

Product Comparison Table

Product Name | U.S. FDA-Approved Product (Infuvite Adult)^1 | Imported Product (Vitalipid N Adult)^2,3 | U.S. FDA-Approved Product (Infuvite Pediatric)^4 | Imported Product (Vitalipid N Infant)^5,6
Manufacturer | Baxter | Fresenius Kabi | Baxter | Fresenius Kabi
Multivitamins & active ingredient salt forms present | 13 vitamins present (water and fat soluble) These include: Thiamine (Vitamin B1) Riboflavin (Vitamin B2) Niacinamide (Vitamin B3) Dexpanthenol (Vitamin B5) Pyridoxine HCl (Vitamin B6) Biotin Folate Cyanocobalamin (Vitamin B12) Ascorbic acid (Vitamin C) Vitamin A (as palmitate) cholecalciferol (Vitamin D3) dl-Alpha-tocopherol acetate (Vitamin E) Vitamin K1 | Only fat-soluble vitamins These include: Retinol palmitate (vitamin A) Ergocalciferol (Vitamin D2) All-rac-Alpha-tocopherol (Vitamin E) Phytomenadione (Vitamin K1) | 13 vitamins present (water and fat soluble) These include: Thiamine (vitamin B1) Riboflavin (vitamin B2) Niacinamide (vitamin B3) Dexpanthenol (vitamin B5) Pyridoxine (vitamin B6) Biotin (B7) Folate (B9) Cyanocobalamin (B12) Ascorbic acid (Vitamin C) Vitamin A (as palmitate) cholecalciferol (Vitamin D3) dl-Alpha-tocopherol acetate (Vitamin E) Vitamin K1 | Only fat-soluble vitamins These include: Retinol palmitate (vitamin A) Ergocalciferol (Vitamin D2) All-rac-Alpha-tocopherol (Vitamin E) Phytomenadione (Vitamin K1)
Differences in the amount of vitamins present in each 1 mL | Ascorbic acid: 20 mg Vitamin A: 330 IU Vitamin D3: 20 IU Thiamine (vitamin B1): 0.6 mg Riboflavin (Vitamin B2): 0.36 mg Pyridoxine (vitamin B6): 0.6 mg Niacinamide: 4 mg Dexpanthenol: 1.5 mg Vitamin E: 1 IU Vitamin K1: 15 mcg Folic Acid: 60 mcg Biotin: 6 mcg Vitamin B12: 0.5 mcg | Ascorbic acid: 0 Vitamin A: 330 IU Vitamin D2: 20 IU Thiamine: 0 Riboflavin:0 Pyridoxine: 0 Niacinamide: 0 Dexpanthenol: 0 Vitamin E: 1 IU Vitamin K1: 15 mcg Folic Acid: 0 Biotin: 0 Vitamin B12: 0 | Ascorbic acid: 16 mg Vitamin A: 460 IU Vitamin D3: 80 IU Thiamine: 0.24 mg Riboflavin: 0.28 mg Pyridoxine: 0.2 mg Niacinamide: 3.4 mg Dexpanthenol: 1 mg Vitamin E: 1.4 IU Vitamin K1: 40 mcg Folic Acid: 28 mcg Biotin: 4 mcg Vitamin B12: 0.2 mcg | Ascorbic acid: 0 Vitamin A: 230 IU Vitamin D2: 40 IU Thiamine: 0 Riboflavin: 0 Pyridoxine: 0 Niacinamide: 0 Dexpanthenol: 0 Vitamin E: 0.7 IU Vitamin K1: 20 mcg Folic Acid: 0 Biotin: 0 Vitamin B12: 0
Package & Container Size | Single dose Vial 1: 5 mL, Vial 2: 5 mL Pharmacy Bulk: Vial 1 – 50 mL, Vial 2 – 50 mL | 10 mL glass ampule, concentrated emulsion for injection | Single dose: Vial 1: 5 mL, Vial 2: 5 mL Pharmacy Bulk: Vial 1 (40 mL Fill in 50 mL Vial) and Vial 2 (10 mL). | 10 mL glass ampule, concentrated emulsion for injection
Storage | Minimize exposure of INFUVITE ADULT to light because vitamins A, D and riboflavin are light sensitive. Store under refrigeration, 2-8°C (36-46°F). | Between 2-25°C (36-77°F). Protect from light. Do not freeze | Minimize exposure of INFUVITE PEDIATRIC to light because vitamins A, D and riboflavin are light sensitive. Store under refrigeration 2-8°C (36-46°F). | Between 2- 25°C (36-77°F). Protect from light. Do not freeze
Shelf Life | Not reported | 24 months | Not reported | 24 months
Excipients | Vial 1: polysorbate 80, sodium hydroxide and/or hydrochloric acid for pH adjustment, water for injection Vial 2: Propylene glycol, citric acid ± sodium citrate for pH, water for injection | Soya oil Egg lecithin Glycerol SWFI NaOH for pH | polysorbate 80, sodium hydroxide and/or hydrochloric acid for pH adjustment, and water for injection. Vial 2: mannitol, citric acid and/or sodium citrate for pH adjustment and water for injection. | Soya oil Egg lecithin Glycerol SWFI NaOH for pH
Aluminum | ≤ 70 mcg/L (vials 1+2) | Not reported | ≤ 30 mcg/L (Vials 1 + 2). | Not reported
Indication | For prevention of vitamin deficiency in adults and children aged 11 and older receiving parenteral nutrition | Indicated in adult patients and children from 11 years of age as a supplement in intravenous nutrition to meet the daily requirements of the fat-soluble vitamins A, D2, E and K1. | For the prevention of vitamin deficiency in pediatric patients up to 11 years of age receiving parenteral nutrition | Indicated in infants and children up to 11 years of age as a supplement in intravenous nutrition to meet the daily requirements of the fat-soluble vitamins A, D2, E and K1.
Dose | 10 mL | 10 mL | <1 kg: 1.5 mL 1 to <3 kg: 3.25 mL ≥3 kg: 5 mL | Preterm and infants below 2.5 kg: 4 mL/kg/d Infants and children >2.5 kg and up to 11 years: 10 mL/d
Contraindications | An existing hypervitaminosis, or A history of hypersensitivity due to any vitamins or excipients contained in this formulation. | Egg, soy, peanut allergy, hypersensitivity to ingredient/excipient | An existing hypervitaminosis, or A history of hypersensitivity to any vitamins or excipients contained in this formulation. | Egg, soy, peanut allergy, hypersensitivity to ingredient/excipient

The following 2 tables compare the content of Infuvite, Vitalipid N and ASPEN Vitamin Recommendations for adult and pediatric patients.

Daily Adult ASPEN Guideline Recommendations for Multivitamins and amount in Vitalipid N Adult and Infuvite Adult Products
 | Adult: Guideline Recommendations^7 | Vitalipid N Adult^2,3 (10 mL dose) | Infuvite Adult^1 (10 mL dose)
Thiamine (B 1) | 6 mg |  | 6 mg
Riboflavin (B 2) | 3.6 mg |  | 3.6 mg
Niacin (B 3) | 40 mg |  | 40 mg
Pantothenic Acid (B 5) | 5 mg |  | 15 mg
Pyridoxine (B 6) | 6 mg |  | 6 mg
Biotin | 60 mcg |  | 60 mcg
Folate | 600 mcg |  | 600 mcg
Cyanocobalamin (B 12) | 5 mcg |  | 5 mcg
Vitamin C (ascorbic acid) | 200 mg |  | 200 mg
Vitamin A | 990 mcg (3300 IU) | 990 mcg (3300 IU) | 3300 IU (1 mg)
Vitamin D | 5 mcg (200 IU) | 5 mcg (200 IU) | 200 IU (5 mcg)
Vitamin E | 10 mg (10 IU) | 9.1 mg (10 IU) | 10 IU (10 mg)
Vitamin K | 150 mcg | 150 mcg | 150 mcg

Daily Pediatric ASPEN Guideline Recommendations for Parenteral Multivitamins and amount in Vitalipid N Infant and Infuvite Pediatric Products
 | Preterm Neonates: Guideline Recommendations | Infants: Guideline Recommendations^7 | Children: Guideline Recommendations^7 | Vitalipid N Infant^5,6 (10 mL) | Infuvite Pediatric (4 mL+ 1 mL)^4
Pediatric Dosing | Amounts/kg/d | Amounts/kg/d | Amounts/d | Preterm and <2.5 kg: 4 mL/kg >2.5 kg to 11 years: 10 mL | < 1 kg: 1.5 mL 1 kg - <3 kg: 3.25 mL ≥ 3 kg: 5 mL
Thiamine (B 1), mg | 200–350 mcg | 0.35 -0.5 | 1.2 |  | 1.2 mg
Riboflavin (B 2, mg) | 50–200 mcg | 0.15 – 0.2 | 1.4 |  | 1.4 mg
Niacin (B 3), mg | 4–6.8 | 4 – 6.8 | 17 |  | 17 mg
Pantothenic Acid (B 5), mg | 1–2 | 1 – 2 | 5 |  | 5 mg
Pyridoxine (B 6), mg | 150–200 mcg | 0.15 – 0.2 | 1 |  | 1 mg
Biotin , mg | 5-8 mcg | 5 – 8 | 20 |  | 20 mcg
Folate, mcg | 56 mcg | 56 | 140 |  | 140 mcg
Cyanocobalamin (B 12), mcg | 0.3 | 0.3 | 1 |  | 1 mcg
Vitamin C (ascorbic acid), mg | 15-25 | 15 – 25 | 80 |  | 80 mg
Vitamin A , mcg (IU) | 700-1500 IU | 150-300 (500 – 1000 IU) | 150 (500 IU) | 690 (2300 IU) | 700 mcg (2300 IU)
Vitamin D, mcg (IU) | 40-160 IU | 0.8 (32 IU) | 10 (400 IU) | 10 mcg (400 IU) | 10 mcg (400 IU)
Vitamin E , mg | 2.8-3.5 IU | 2.8 – 3.5 | 7 | 6.4 mg (7 IU) | 7 mg (7 IU)
Vitamin K 1 , mcg | 10 | 10 | 200 | 200 mcg | 200 mcg

Refer to the Vitalipid N package insert for full prescribing information

REPORTING ADVERSE EVENTS

To report adverse events experienced with the use of this product, call Fresenius Kabi USA Vigilance at 1-800-551-7176, Monday – Friday, between the hours of 8 a.m. and 5 p.m. (CST), or e-mail adverse.events.USA@fresenius-kabi.com

To report a product complaint with the use of this product, call (800) 551- 7176 or e-mail productcomplaint.USA@fresenius-kabi.com.

Fresenius Kabi USA CONTACT NUMBERS: Please use the following contact numbers as appropriate:

Reason To Call | Department | Number
ADE Reporting | Vigilance Department | 1-800-551-7176
Clinical/Technical Info. Or Product Complaint | Medical Affairs Department | 1-800-551-7176
Product Availability & Ordering | Customer Service Department | 1-888-386-1300

Adverse reactions or quality problems experienced with the use of this product may be reported to the FDA's MedWatch Adverse Event Reporting program either online, by regular mail or by fax.

- Complete and submit the report Online: www.fda.gov/medwatch/report.htm
- Regular Mail or Fax: Download form www.fda.gov/medwatch/getforms.htm or call 1-800-332-1088 to request a reporting form, then complete and return to the address on the pre-addressed form, or submit by fax to 1-800-FDA-0178 (1-800-332-0178).

Sincerely,

Gordon S. Sacks, PharmD, BCNSP, FASPEN, FCCP
Senior Director, Medical Affairs
Fresenius Kabi USA, LLC

Vitalipid N and Vitlipid N, Infuvite Pediatric and Infuvite Adult Product Labels
Product | Shipper label | Box Label | Ampule/Vial label | Ampule/Vial picture
Vitalipid N Infant
Vitlipid N Infant |  |  |  | Not available
Infuvite Pediatric (Baxter Healthcare) | Not available |  | Not available
Vitlipid N Adult |  |  |  | Not available
Infuvite Adult (Baxter Healthcare) | Not available

References:

1. Infuvite Adult. Prescribing Information. Baxter Healthcare Corporation. Deerfield IL. October 2016.
2. Vitalipid N Adult Summary of Product Characteristics. Fresenius Kabi 2008
3. Vitalipid N Adult Prescribing Information, Fresenius Kabi AB. Uppsala, Sweden
4. Infuvite Pediatric. Prescribing Information. Baxter Healthcare Corporation. Deerfield IL. October 2016.
5. Vitalipid N Infant Prescribing Information, Fresenius Kabi AB. Uppsala, Sweden
6. Vitalipid N Infant Summary of Product Characteristics. Fresenius Kabi 2008
7. Vanek VW, Borum P, Buchman A, et al. A.S.P.E.N. Position Paper: Recommendations for changes in commercially available parenteral multivitamin and multi-trace element products. Nutr Clin Pract. 2012;27(4):440-491.

PACKAGE LABEL

PACKAGE LABEL – PRINCIPAL DISPLAY PANEL – VITALIPID® N Infant 10 mL Ampule Label

Vitalipid® N Infant 10 ml

Concentrate for emulsion for infusion

For intravenous infusion

PACKAGE LABEL

PACKAGE LABEL – PRINCIPAL DISPLAY PANEL – VITALIPID® N Infant 10 mL Ampule Carton Panel

Vitalipid® N Infant

Concentrate for emulsion for infusion

For intravenous infusion

PACKAGE LABEL

PACKAGE LABEL – PRINCIPAL DISPLAY PANEL – VITALIPID™ N Infant 10 mL Ampule Label

Vitalipid™ N Infant 10 ml

Concentrate for solution for infusion, emulsion

PACKAGE LABEL

PACKAGE LABEL – PRINCIPAL DISPLAY PANEL – VITALIPID™ N Infant 10 mL Ampule Carton Panel

Vitalipid™ N Infant

Concentrate for solution for infusion

PACKAGE LABEL

PACKAGE LABEL – PRINCIPAL DISPLAY PANEL – VITALIPID® N Adult 10 mL Ampule Label

Vitalipid® N Adult 10 ml

Concentrate for emulsion for infusion

For intravenous infusion

PACKAGE LABEL

PACKAGE LABEL – PRINCIPAL DISPLAY PANEL – VITALIPID® N Adult 10 mL Ampule Carton Panel

Vitalipid® N Adult

Concentrate for emulsion for infusion

For intravenous infusion